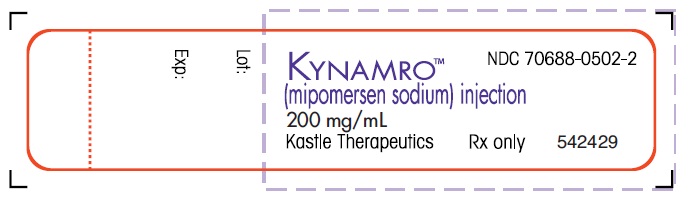 DRUG LABEL: Kynamro
NDC: 70688-0502 | Form: INJECTION, SOLUTION
Manufacturer: Kastle Therapeutics, LLC
Category: prescription | Type: HUMAN PRESCRIPTION DRUG LABEL
Date: 20170117

ACTIVE INGREDIENTS: MIPOMERSEN SODIUM 200 mg/1 mL
INACTIVE INGREDIENTS: WATER; HYDROCHLORIC ACID; SODIUM HYDROXIDE

KYNAMRO- MIPOMERSEN SODIUM INJECTION, SOLUTION